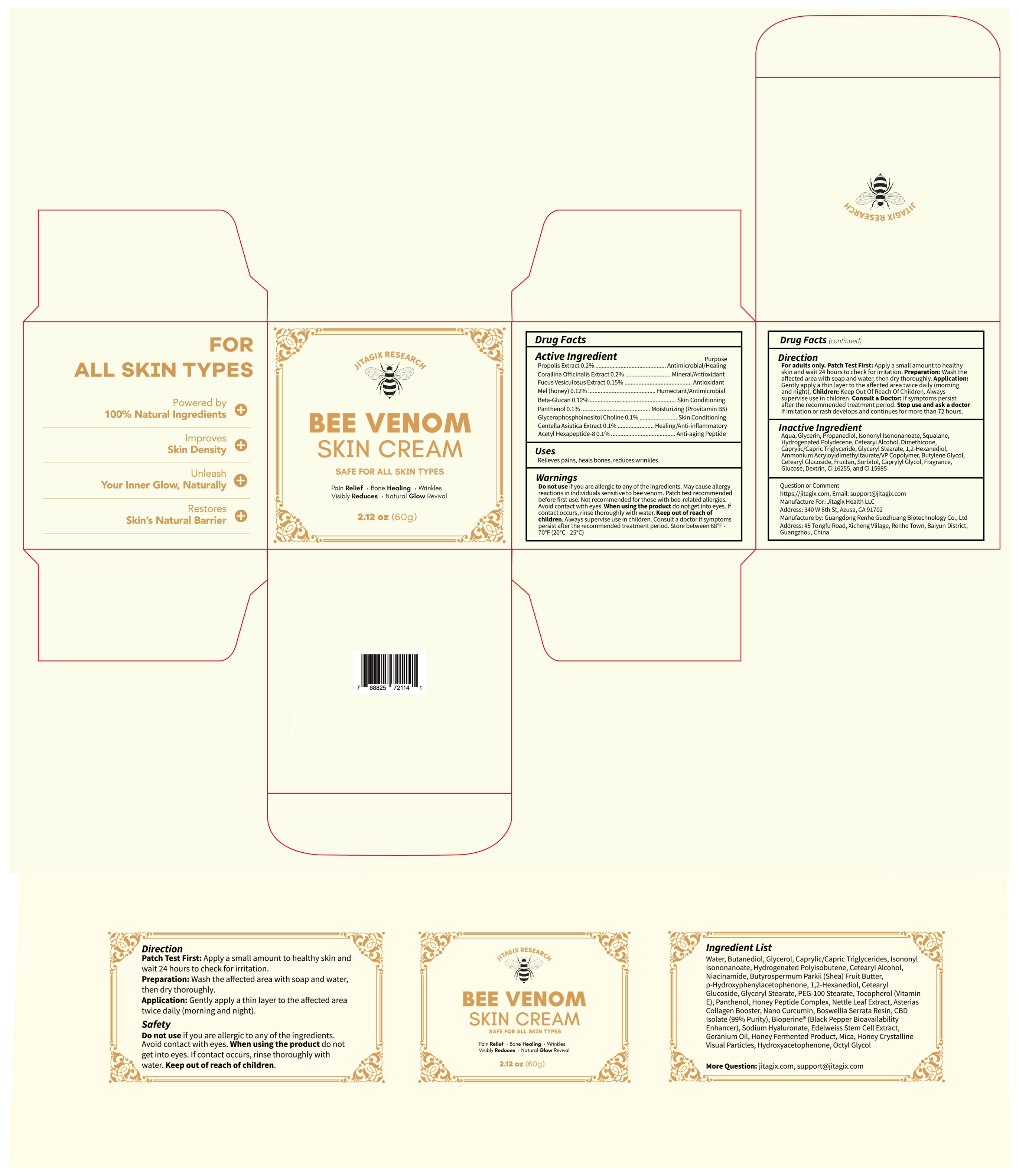 DRUG LABEL: JITAGIX BEE VENOM Skin Cream
NDC: 85587-006 | Form: CREAM
Manufacturer: Shenzhen Zealous Ecommerce Technology Co., Ltd
Category: otc | Type: HUMAN OTC DRUG LABEL
Date: 20250818

ACTIVE INGREDIENTS: SODIUM CARBOXYMETHYL .BETA.-GLUCAN (DS 0.65-0.85) 0.12 g/100 g; PANTHENOL 0.1 g/100 g; CORALLINA OFFICINALIS 0.2 g/100 g; ACETYL HEXAPEPTIDE-8 0.1 g/100 g; MEL 0.12 g/100 g; PROPOLIS CERA 0.2 g/100 g; FUCUS VESICULOSUS 0.15 g/100 g; GLYCEROPHOSPHOINOSITOL CHOLINE 0.1 g/100 g; CENTELLA ASIATICA TRITERPENOIDS 0.1 g/100 g
INACTIVE INGREDIENTS: CAPRYLYL GLYCOL; DEXTRIN, CORN; DIMETHICONE; CAPRYLIC/CAPRIC TRIGLYCERIDE; GLYCERYL STEARATE; SORBITOL; GLUCOSE; FRUCTOSE; AMMONIUM ACRYLOYLDIMETHYLTAURATE/VP COPOLYMER; CETEARYL GLUCOSIDE; PROPANEDIOL; SQUALANE; ISONONYL ISONONANOATE; HYDROGENATED POLYDECENE TYPE I; FRAGRANCE 13576; 1,2-HEXANEDIOL; BUTYLENE GLYCOL; CI 15985; GLYCERIN; CETEARYL ALCOHOL; CI 16255; AQUA

85587-006

Active Ingredient

Propolis Extract 0.2%, Corallina Officinalis Extract 0.2%, Fucus Vesiculosus Extract 0.15%, Mel (honey) 0.12%, Beta-Glucan 0.12%, Panthenol 0.1%, Glycerophosphoinositol Choline 0.1%, Centella Asiatica Extract 0.1%, Acetyl Hexapeptide-8 0.1%

Purpose

Pain Relief, Bone Healing, Wrinkles Reduces

Use

Use 1-2 time per day.

Warnings

Patch test recommended before first use. Avoid contact with eyes. Not recommended for those with bee-related allergies.

Do not use

Not recommended for those with bee-related allergies.

When Using

Patch test recommended before first use.

Stop Use

Stop use if symptoms persist after the recommended treatment period.

Ask Doctor

Consult a doctor if symptoms persist after the recommended treatment period.

Keep Out Of Reach Of Children

Directions

Apply a pea-sized amount to cleansed face and neck every morning and night.
Gently massage upward in circular motions.
Follow with SPF (daytime).

Inactive ingredients

AQUA, GLYCERIN, PROPANEDIOL, ISONONYL ISONONANOATE, SQUAL-ANE, HYDROGENATED POLYDECENE, CETEARYL ALCOHOL, DIMETHICONE, CAPRYLIC/CAPRIC TRIGLYCERIDE, GLYCERYL STEARATE 1,2-HEXANEDIOL, AMMONIUM ACRYLOYLDIMETHYLTAURATENP COPO. LYMER, BUTYLENE GLYCOL, CETEARYL GLUCOSIDE, FRUCTAN, PROPOLIS EXTRACT, SORBITOL, CAPRYLYL GLYCOL, FRAGRANCE, CORALLINA OFFI CINALIS EXTRACT, FUCUS VESICULOSUS EXTRACT, MEL, GLUCOSE, BETA-GLUCAN, PANTHENOL, GLYCEROPHOSPHOINOSITOL CHOLINE, DEXTRIN, CI 16255, CI 15985, CENTELLA ASIATICA EXTRACT, ACETYL HEXAPEPTIDE

Questions

Email: support@jitagix.com